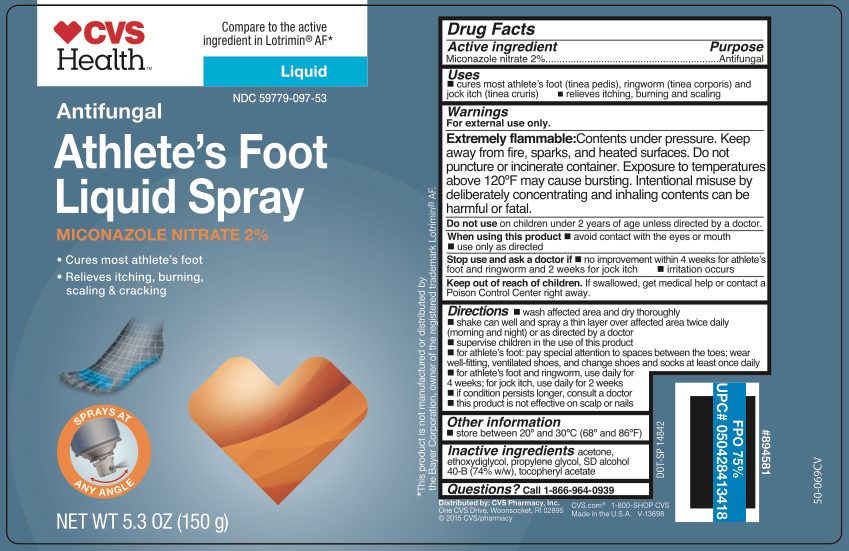 DRUG LABEL: Miconazole Nitrate
NDC: 59779-097 | Form: AEROSOL, SPRAY
Manufacturer: CVS Pharmacy
Category: otc | Type: HUMAN OTC DRUG LABEL
Date: 20260210

ACTIVE INGREDIENTS: MICONAZOLE NITRATE 3 g/150 g
INACTIVE INGREDIENTS: ETHOXYDIGLYCOL; PROPYLENE GLYCOL; ALCOHOL; .ALPHA.-TOCOPHEROL ACETATE; ACETONE

CVS Miconazole Liquid Spray Athlete's Foot Spray

Active ingredient

Miconazole nitrate 2%

Purpose

Antifungal

Uses

- cures most athlete's foot (linea pedis), ringworm (linea corporis) and jock itch (linea cruris)
- relieves itching, burning and scaling

Warnings

For external use only.

Extremely flammable:

Contents under pressure. Keep away from fire, sparks, and heated surfaces. Do not puncture or incinerate container. Exposure to temperatures above 120°F may cause bursting. Intentional misuse by deliberately concentrating and inhaling contents can be harmful or fatal.

Do not use

on children under 2 years of age unless directed by a doctor.

When using this product

- avoid contact with the eyes or mouth
- use only as directed

Stop use and ask a doctor if

- no improvement within 4 weeks for athlete's foot and ringworm and 2 weeks for jock itch
- irritation occurs

Keep out of reach of children.

If swallowed, get medical help or contact a Poison Control Center right away.

Directions

- wash affected area and dry thoroughly
- shake can well and spray a thin layer over affected area twice daily (morning and night) or as directed by a doctor
- supervise children in the use of this productfor athlete's foot: pay special attention to spaces between the toes; wear well-fitting, ventilated shoes, and change shoes and socks at least once daily
- for athlete's foot and ringworm, use daily for 4 weeks; for jock itch, use daily for 2 weeks
- if conditions persist, consult a doctor
- this product is not effective on the scalp or nails

Other information

store between 20º and 30ºC (68ºF and 86º)

Inactive ingredients

acetone, ethoxydiglycol, propylene glycol, SD alcohol 40-B (74% w/w), tocopheryl acetate

Questions?

call 1-866-964-0939

RECENT MAJOR CHANGES

.

Principal Display Panel

CVS

Health

Antifungal

Athlete's Foot
Liquid Spray

Miconazole Nitrate 2%

- Cures most athlete's foot
- Relieves itching, burning,

scaling & cracking

NET WT 5.3 OZ (150g)